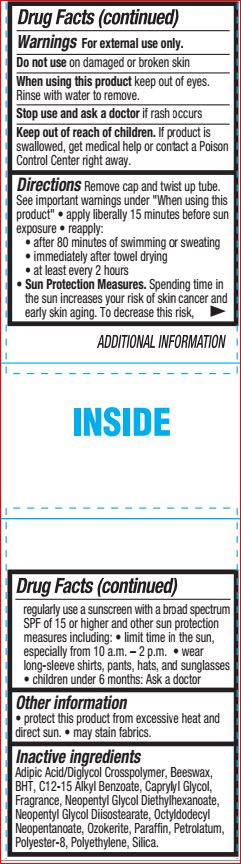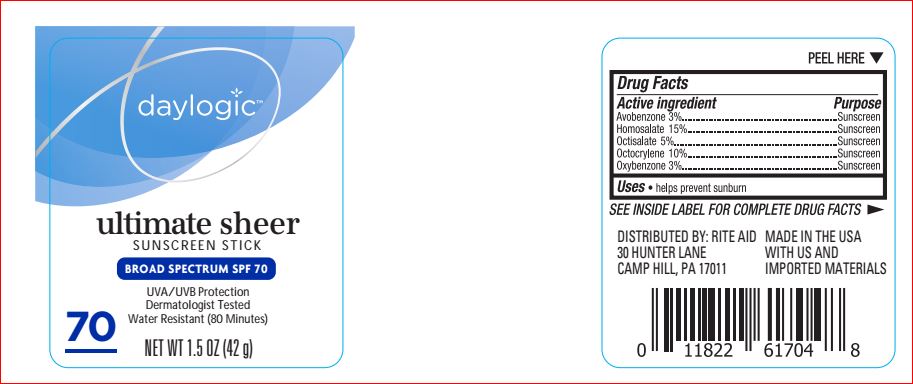 DRUG LABEL: Ultimate Sheer Sunscreen  SPF 70
NDC: 64048-1235 | Form: STICK
Manufacturer: Product Quiest Mfg
Category: otc | Type: HUMAN OTC DRUG LABEL
Date: 20180619

ACTIVE INGREDIENTS: Avobenzone 3 g/100 g; Homosalate 15 g/100 g; Octisalate 5 g/100 g; Octocrylene 10 g/100 g; Oxybenzone 3 g/100 g
INACTIVE INGREDIENTS: YELLOW WAX; BUTYLATED HYDROXYTOLUENE; ALKYL (C12-15) BENZOATE; Caprylyl Glycol; NEOPENTYL GLYCOL DIETHYLHEXANOATE; Neopentyl Glycol Diisostearate; Octyldodecyl Neopentanoate; CERESIN; Paraffin; Petrolatum; POLYESTER-8 (1400 MW, CYANODIPHENYLPROPENOYL CAPPED); HIGH DENSITY POLYETHYLENE; SILICON DIOXIDE

Drug Facts